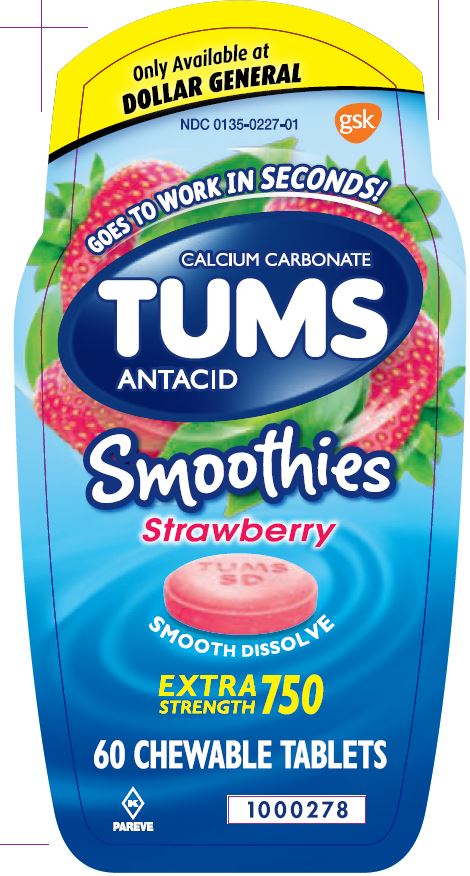 DRUG LABEL: TUMS

NDC: 0135-0227 | Form: TABLET, CHEWABLE
Manufacturer: Haleon US Holdings LLC
Category: otc | Type: HUMAN OTC DRUG LABEL
Date: 20240303

ACTIVE INGREDIENTS: CALCIUM CARBONATE 750 mg/1 1
INACTIVE INGREDIENTS: ACACIA; ADIPIC ACID; CALCIUM STEARATE; DEXTROSE, UNSPECIFIED FORM; FD&C RED NO. 40; GUAR GUM; MICROCRYSTALLINE CELLULOSE; SORBITOL

Drug Facts

Active ingredient (per tablet)

Calcium Carbonate 750 mg

Purpose

Antacid

Uses

relieves

- heartburn
- acid indigestion
- sour stomach
- upset stomach associated with these symptoms

Warnings

Ask a doctor or pharmacist before use if you are

presently taking a prescription drug. Antacids may interact with certain prescription drugs.

When using this product

- do not take more than 10 tablets in 24 hours
- if pregnant do not take more than 6 tablets in 24 hours
- do not use the maximum dosage for more than 2 weeks except under the advice and supervision of a doctor

Directions

- adults and children 12 years of age and over:chew 2 – 4 tablets as symptoms occur, or as directed by a doctor
- do not take for symptoms that persist for more than 2 weeks unless advised by a doctor

Other information

- each tablet contains:elemental calcium 300mg
- do not store above 25oC (77oF). Keep the container tightly closed.

Inactive ingredients

acacia, adipic acid, calcium stearate, dextrose, FD&C red no. 40 aluminum lake, flavors, guar gum, microcrystalline cellulose, sorbitol

Questions or comments?

1-800-897-7535

Principal Display Panel

NDC 0135-0227-01

TUMS

CALCIUM CARBONATE

ANTACID

Smoothies

Strawberry

SMOOTH DISSOLVE

EXTRA STRENGTH 750

GOES TO WORK IN SECONDS!

60 CHEWABLE TABLETS

Only Available at DOLLAR GENERAL

PAREVE

Do not use if printed inner safety seal under cap is broken or missing.

Dist. By: GSK CH

Warren, NJ 07059

©2019 GSK or licensor.

Front Panel 1000278